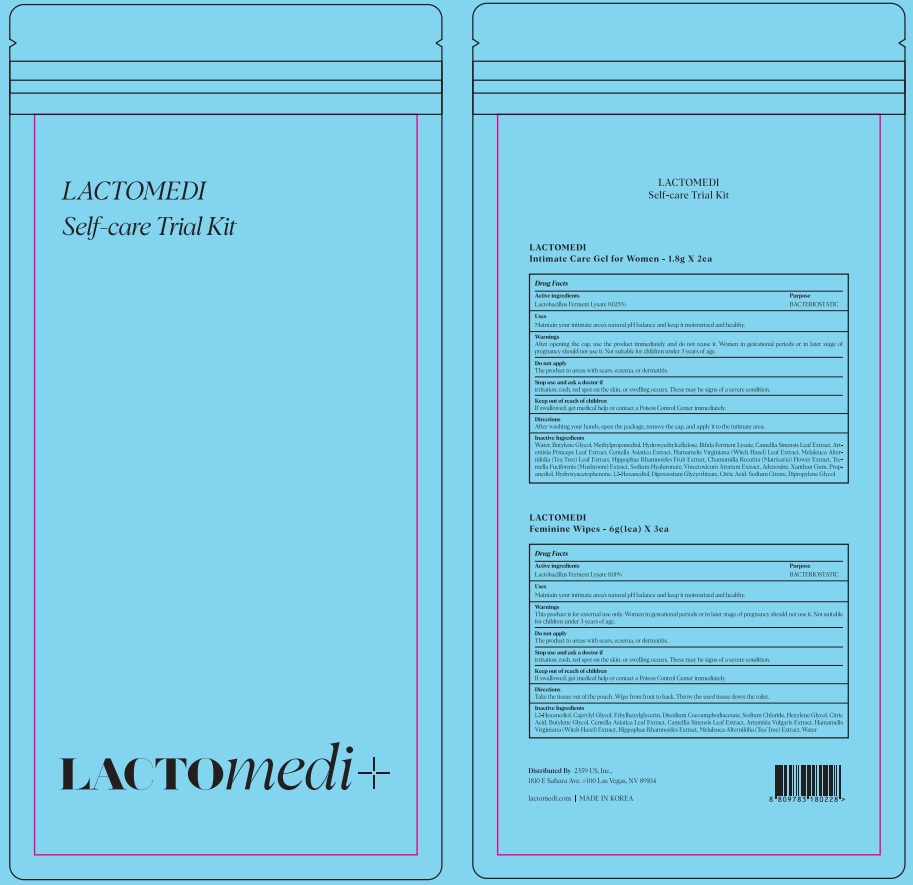 DRUG LABEL: Lactomedi Self-care Trial Kit
NDC: 83490-901 | Form: KIT | Route: TOPICAL
Manufacturer: 2359 US INC
Category: otc | Type: HUMAN OTC DRUG LABEL
Date: 20230424

ACTIVE INGREDIENTS: LIMOSILACTOBACILLUS FERMENTUM ME-3 0.01 g/100 g; LIMOSILACTOBACILLUS FERMENTUM ME-3 0.025 g/100 g
INACTIVE INGREDIENTS: CENTELLA ASIATICA LEAF; WATER; GREEN TEA LEAF; CAPRYLYL GLYCOL; CITRIC ACID MONOHYDRATE; HAMAMELIS VIRGINIANA TOP; HIPPOPHAE RHAMNOIDES FRUIT; HEXYLENE GLYCOL; 1,2-HEXANEDIOL; DISODIUM COCOAMPHODIACETATE; SODIUM CHLORIDE; ETHYLHEXYLGLYCERIN; ARTEMISIA VULGARIS WHOLE; MELALEUCA ALTERNIFOLIA WHOLE; BUTYLENE GLYCOL; HYDROXYETHYL CELLULOSE, UNSPECIFIED; HYALURONATE SODIUM; TREMELLA FUCIFORMIS WHOLE; VINCETOXICUM ATRATUM WHOLE; XANTHAN GUM; HYDROXYACETOPHENONE; ARTEMISIA PRINCEPS LEAF; WATER; CENTELLA ASIATICA TRITERPENOIDS; METHYLPROPANEDIOL; MELALEUCA ALTERNIFOLIA LEAF; CHAMOMILE; HAMAMELIS VIRGINIANA LEAF; HIPPOPHAE RHAMNOIDES FRUIT; ACONITIC ACID; SODIUM CITRATE; DIPROPYLENE GLYCOL; BUTYLENE GLYCOL; PROPANEDIOL; ADENOSINE; 1,2-HEXANEDIOL; GREEN TEA LEAF; GLYCYRRHIZINATE DIPOTASSIUM

83490-901 Lactomedi Self-care Trial Kit

Active Ingredients

Lactobacillus Ferment Lysate

Purposes

BACTERIOSTATIC

Uses

Maintain your natural pH balance and keep your intimate area moist.

Warnings

Do not use it on the part where you have a scar, eczema, or dermatitis.

Do not suitable for children under 3 years of age

Warnings

Keep out of reach of children
If swallowed, get medical help or contact a Poison Control Center immediately.

Warnings

Stop use and ask a doctor if
irritation, rash, red spot on the skin, or swelling occurs. These may be signs of a severe condition.

Warnings

After opening the cap, use the product immediately and do not reuse it. Women in gestational periods should better not use it and not use it on the vulva just before delivery.

Women in gestational periods should better not use it and not use it on the vulva just before delivery.

Warnings

After opening the cap, use the product immediately and do not reuse it.

Directions

After washing your hands, open the package, remove the cap, and apply it to the intimate area as if it were an injection.

Take the tissue out of the pouch. Wipe the are from front to back. Throw tissue s in the toilet.

Inactive Ingredients

Water, Butylene Glycol, Methylpropanediol, Hydroxyethylcellulose, Bifida Ferment Lysate, Camellia Sinensis Leaf Extract, Artemisia Princeps Leaf Extract, Centella Asiatica Extract, Hamamelis Virginiana (Witch Hazel) Leaf Extract, Melaleuca Alternifolia (Tea Tree) Leaf Extract, Hippophae Rham- noides Fruit Extract, Chamomilla Recutita (Matricaria) Flower Extract, Tre- mella Fuciformis (Mushroom) Extract, Sodium Hyaluronate, Vincetoxicum Atratum Extract, Adenosine, Xanthan Gum, Propanediol, Hydroxyacetoph enone,1,2-Hexanediol, Dipotassium Glycyrrhizate, Citric Acid,Sodium Citr- ate, Dipropylene Glycol

1,2-Hexanediol, Caprylyl Glycol, Ethylhexylglycerin, Disodium Cocoamphodiace- tate, Sodium Chloride, Hexylene Glycol, Citric Acid, Butylene Glycol, Centella Asiatica Leaf Extract, Camellia Sinensis Leaf Extract, Artemisia Vulgaris Extract, Hamamelis Virginiana (Witch Hazel) Extract, Hippophae Rhamnoides Extract, Melaleuca Alternifolia (Tea Tree) Extract, Water